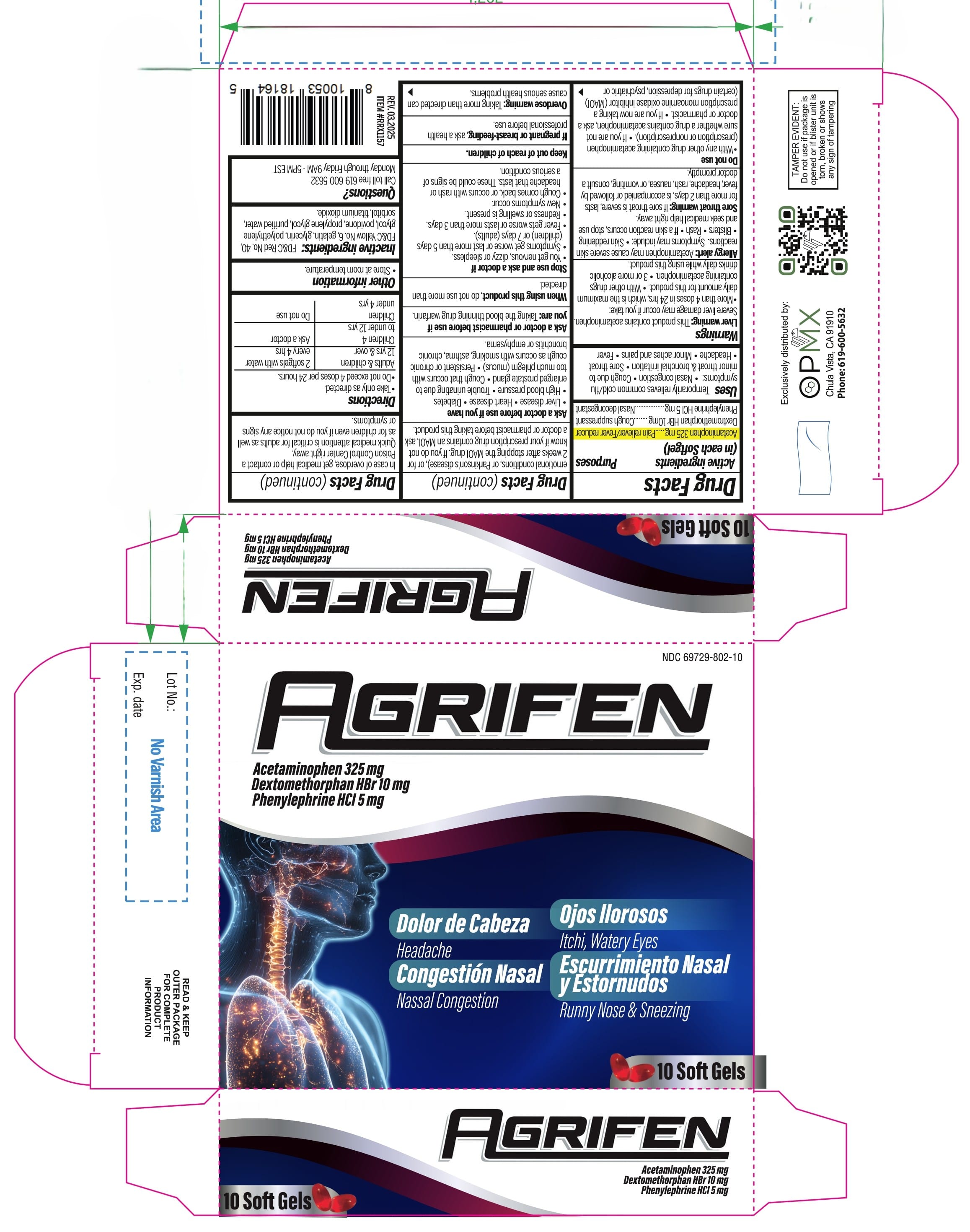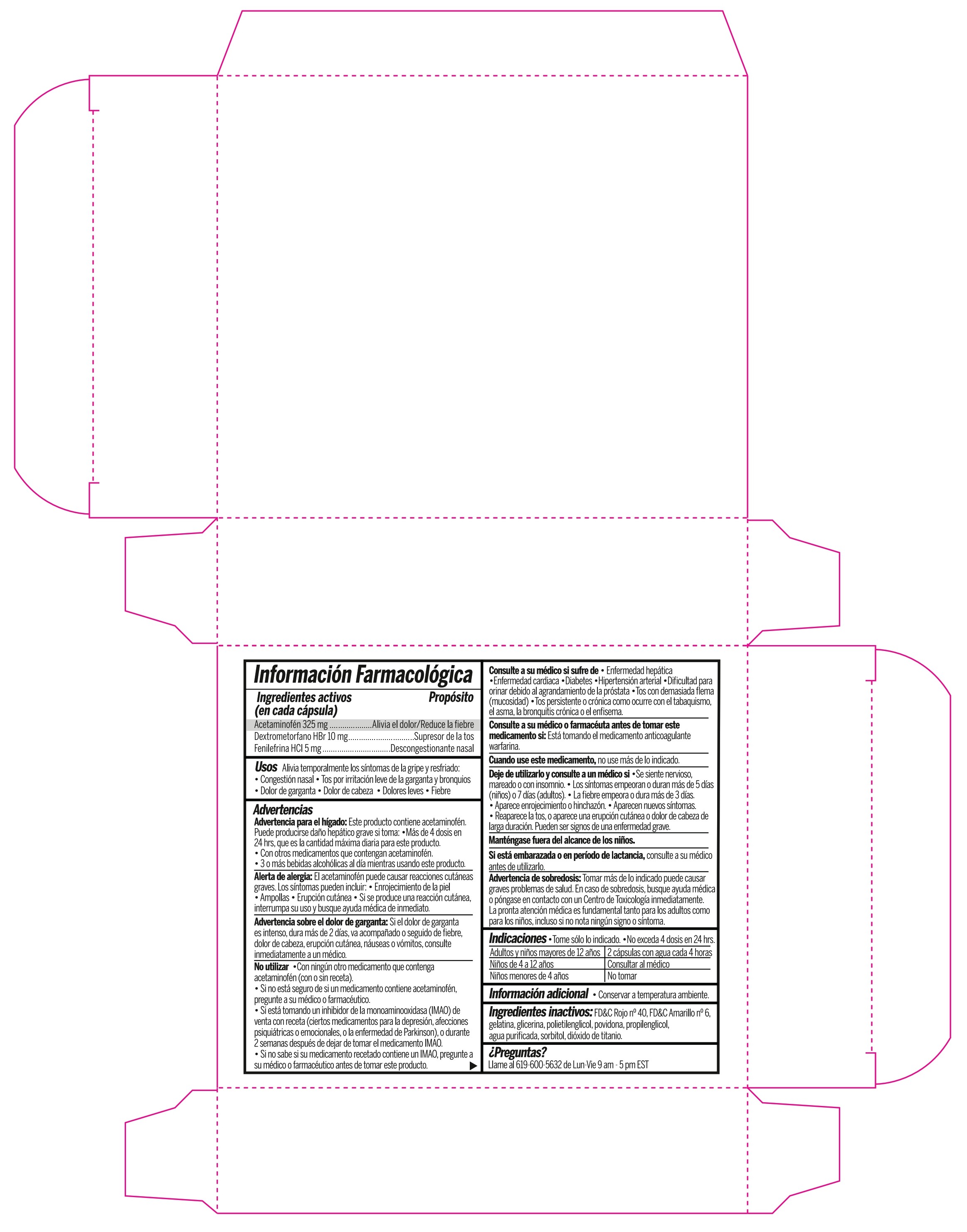 DRUG LABEL: AGRIFEN
NDC: 69729-802 | Form: CAPSULE, LIQUID FILLED
Manufacturer: OPMX LLC
Category: otc | Type: HUMAN OTC DRUG LABEL
Date: 20250331

ACTIVE INGREDIENTS: ACETAMINOPHEN 325 mg/1 1; PHENYLEPHRINE HYDROCHLORIDE 5 mg/1 1; DEXTROMETHORPHAN HYDROBROMIDE 10 mg/1 1
INACTIVE INGREDIENTS: FD&C RED NO. 40; PROPYLENE GLYCOL; GLYCERIN; WATER; POVIDONE; SORBITOL; FD&C YELLOW NO. 6; POLYETHYLENE GLYCOL, UNSPECIFIED; GELATIN; TITANIUM DIOXIDE

AGRIFEN

Active ingredient

Active ingredients (in each Softgel) | Purposes
Acetaminophen 325 mg | Pain reliever/Fever reducer
Dextromethorphan HBr 10 mg | Cough suppressant
Phenylephrine HCl 5mg | Nasal descongestant

Uses

Temporarily relieves common cold/flu symptoms:

- Nasal congestion
- Cough due to minor throat & bronchial irritation
- Sore throat
- Headache
- Minor aches and pains
- Fever

Uses

- Pain reliever/Fever reducer
- Cough suppressant
- Nasal descongestant

Warnings

Liver warning: This product contains acetaminophen. Severe liver damage may occur if you take:

- More than 4 doses in 24 hrs, which is the maximum daily amount for this product.
- With other drugs containing acetaminophen.
- 3 or more alcoholic drinks daily while using this product

Allergy alert: Acetaminophen may cause severe skin reactions. Symptoms may include:

- Skin reddening
- Blisters
- Rash
- If a skin reactions occurs, stop use and seek medical help right away

Sore throat warning: If sore throat is severe, lasts for more than 2 days, is accompained or followed by fever, headache, rash, nausea, or vomiting, consult a doctor promptly

Do not use

- With any other drug containing acetaminophen (prescription or nonprescription)
- If you are not sure whether a drug contains acetaminophen, ask a doctor or pharmacist
- If you are now taking a prescription monoamine oxidase inhibitor (MAOI)(certain drugs for depression, psychiatric or emotional conditions, or Parkinson´s disease), or for 2 weeks after stopping the MAOI drug. If you do not know if your prescription drug contains an MAOI, ask a doctor or pharmacist before taking this product.

Ask a doctor before use if you have

- Liver disease
- Hear disease
- Diabetes
- High blood pressure
- Trouble urinating due to enlarged prostate gland
- Cough that occurs with too mcuh plegm (mucus)
- Persistent or chronic cough occurs with smoking, asthma, chronic bronchitis or emphysema

Ask a doctor or pharmacist before use if you are:

Taking the blood thinning drug warfarin.

When using this product,

do not use more than directed.

Stop use and ask a doctor if

- You get nervous, dizzy or sleepless
- Symptoms get worse or last more than 5 days (children) or 7 days (adults)
- Fever gets worse or lasts more than 3 days
- Redness or swelling is present
- New symptoms occur
- Cough comes back, or occurs with rash or headache that lasts. These could be signs of a serious condition

If pregnant or breast-feeding

ask a health professional before use.

Overdose warning:

Taking more than directed can cause serious health problems. In case of overdose, get medical help or contact a Poison Control Center right away.

Quick medical attention is critical for adults as well as for children even if you dot notice any signs or symptoms.

Directions

- Take only as directed.
- Do not exceed 4 doses per 24 hours.

Adults & children 12 yrs & over | 2 softgels with water every 4 hrs
Children 4 to under 12 yrs | Ask a doctor
Children under 4 yrs | Do not use

Other information

- Store at room temperature.

Inactive ingredients

FD&C Red No.40, FD&C Yellow No. 6, gelatin, glycerin, polyethylene glycol, povidone, propylene glycol, purified water, sorbitol, titanium dioxide.

Questions?

Call toll free 619-600-5632

Monday through Friday 9AM - 5PM EST

PACKAGE LABEL

NDC 69729-802-10

AGRIFEN

Acetaminophen 325 mg

Dextomethorphan HBr 10 mg

Phenylephrine HCl 5 mg

Dolor de Cabeza

Headache

Congestión Nasal

Nassal Congestion

Ojos llorosos

Itchi, Watery eyes

Escurrimiento Nasal y Estornudos

Runny Nose & Sneezing

10 Soft Gels

Exclusively distributes by:

OPMX

Chula Vista, CA 91910

Phine: 619-600-5632

TAMPER EVIDENT:

Do not use if package is opened or if blister unit is torn, broken or shows any sign of tampering